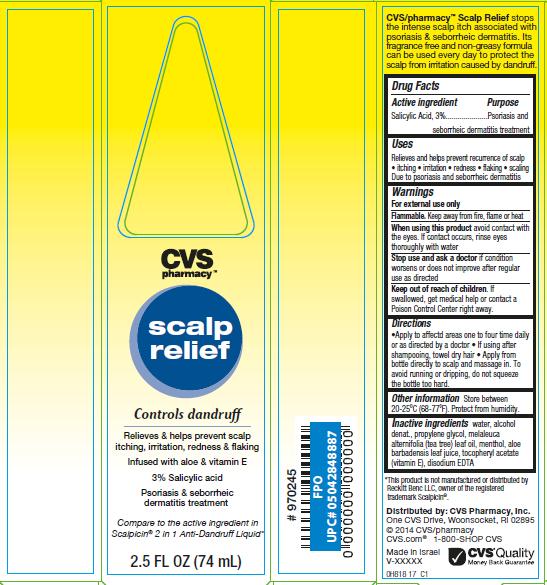 DRUG LABEL: CVS Scalp Relief
NDC: 59779-818 | Form: LIQUID
Manufacturer: CVS Pharmacy
Category: otc | Type: HUMAN OTC DRUG LABEL
Date: 20140521

ACTIVE INGREDIENTS: SALICYLIC ACID 3 g/100 mL
INACTIVE INGREDIENTS: WATER; ALCOHOL; PROPYLENE GLYCOL; TEA TREE OIL; MENTHOL; ALOE VERA LEAF; .ALPHA.-TOCOPHEROL ACETATE; EDETATE DISODIUM

CVS pharmacy™ scalp relief

Active ingredient

Salicylic Acid, 3%

Purpose

Psoriasis and seborrheic dermatitis treatment

Uses

Relieves and helps prevent recurrence of scalp

- itching
- irritation
- redness
- flaking
- scaling

Due to psoriasis and seborrheic dermatitis

Warnings

For external use only.

Flammable.

Keep away from fire, flame or heat

When using this product

avoid contact with the eyes. If contact occurs, rinse eyes thoroughly with water

Stop use and ask a doctor

if condition worsens or does not improve after regular use as directed

Keep Out of Reach of Children.

If swallowed, get medical help or contact a Poison Control Center right away.

Directions

- Apply to affected areas one to four times daily or as directed by a doctor
- If using after shampooing, towel dry hair
- Apply from bottle directly to scalp and massage in. To avoid running or dripping, do not squeeze the bottle too hard.

Other Information

Store between 20-25°C (68-77°F). Protect from humidity.

Inactive Ingredients

water, alcohol denat., propylene glycol, melaleuca alternifolia (tea tree) leaf oil, menthol, aloe barbadensis leaf juice, tocopheryl acetate (vitamin E), disodium EDTA

Package/Label Principal Display Panel - Carton Label

CVS pharmacy™

scalp relief

Controls dandruff

Relieves and helps prevent scalp itching, irritation, redness and flaking

Infused with aloe and vitamin E

3% Salicylic acid

Psoriasis and seborrheic dermatitis treatment

Compare to the active ingredient in Scalpicin® 2 in 1 Anti-Dandruff Liquid*

2.5 FL OZ (74 mL)

*This product is not manufactured or distributed by Reckitt Benc LLC, owner of the registered trademark Scalpicin®.

CVS/pharmacy™ Scalp Relief stops the intense scalp itch associated with psoriasis and seborrheic dermatitis. Its fragrance free and non-greasy formula can be used every day to protect the scalp from irritation caused by dandruff.

Carton Label